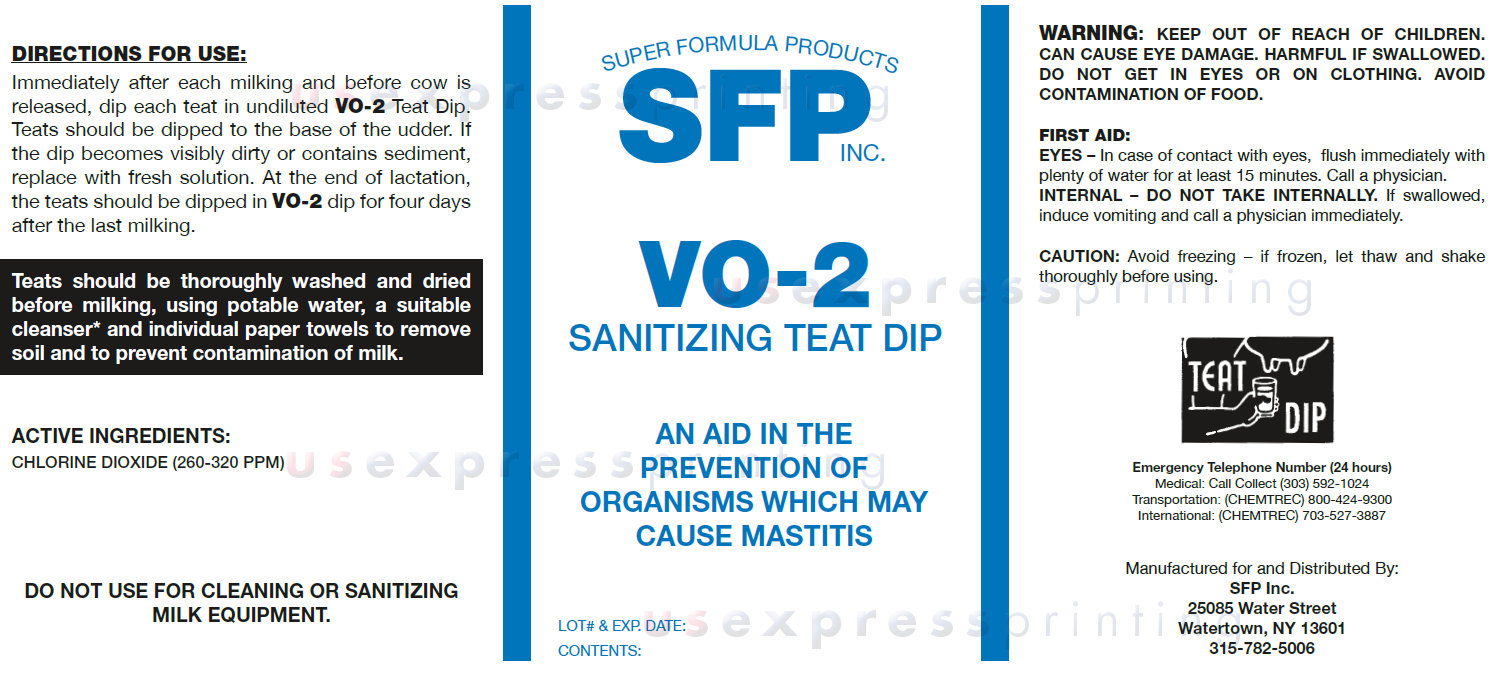 DRUG LABEL: SFP INC. VO-2 SANITIZING TEAT DIP
NDC: 35723-104 | Form: LIQUID
Manufacturer: SUPER FORMULA PRODUCTS INC.
Category: animal | Type: OTC ANIMAL DRUG LABEL
Date: 20140723

ACTIVE INGREDIENTS: CHLORINE DIOXIDE 320 mg/1 L

SFP INC. VO-2 SANITIZING TEAT DIP

DIRECTIONS FOR USE:

Immediately after each milking and before cow is released, dip each teat in undiluted VO-2 Teat Dip. Teats should be dipped to the base of the udder. If the dip becomes visibly dirty or contains sediment, replace with fresh solution. At the end of lactation, the teats should be dipped in VO-2 dip for four days after the last milking.
Teats should be thoroughly washed and dried before milking, using potable water, a suitable cleanser* and individual paper towels to remove soil and to prevent contamination of milk.

ACTIVE INGREDIENTS:

CHLORINE DIOXIDE (260-320 PPM)

DO NOT USE FOR CLEANING OR SANITIZING MILK EQUIPMENT.

WARNINGS AND PRECAUTIONS

WARNING: Keep Out Of Reach Of Children. Can Cause Eye Damage. Harmful If Swallowed . DO NOT get in eyes or on clothing. Avoid Contamination Of Food.
FIRST AID:
EYES – In case of contact with eyes, flush immediately with plenty of water for at least 15 minutes. Call a physician.
INTERNAL – DO NOT TAKE INTERNALLY. If swallowed, induce vomiting and call a physician immediately.
CAUTION: Avoid freezing – if frozen, let thaw and shake thoroughly before using.